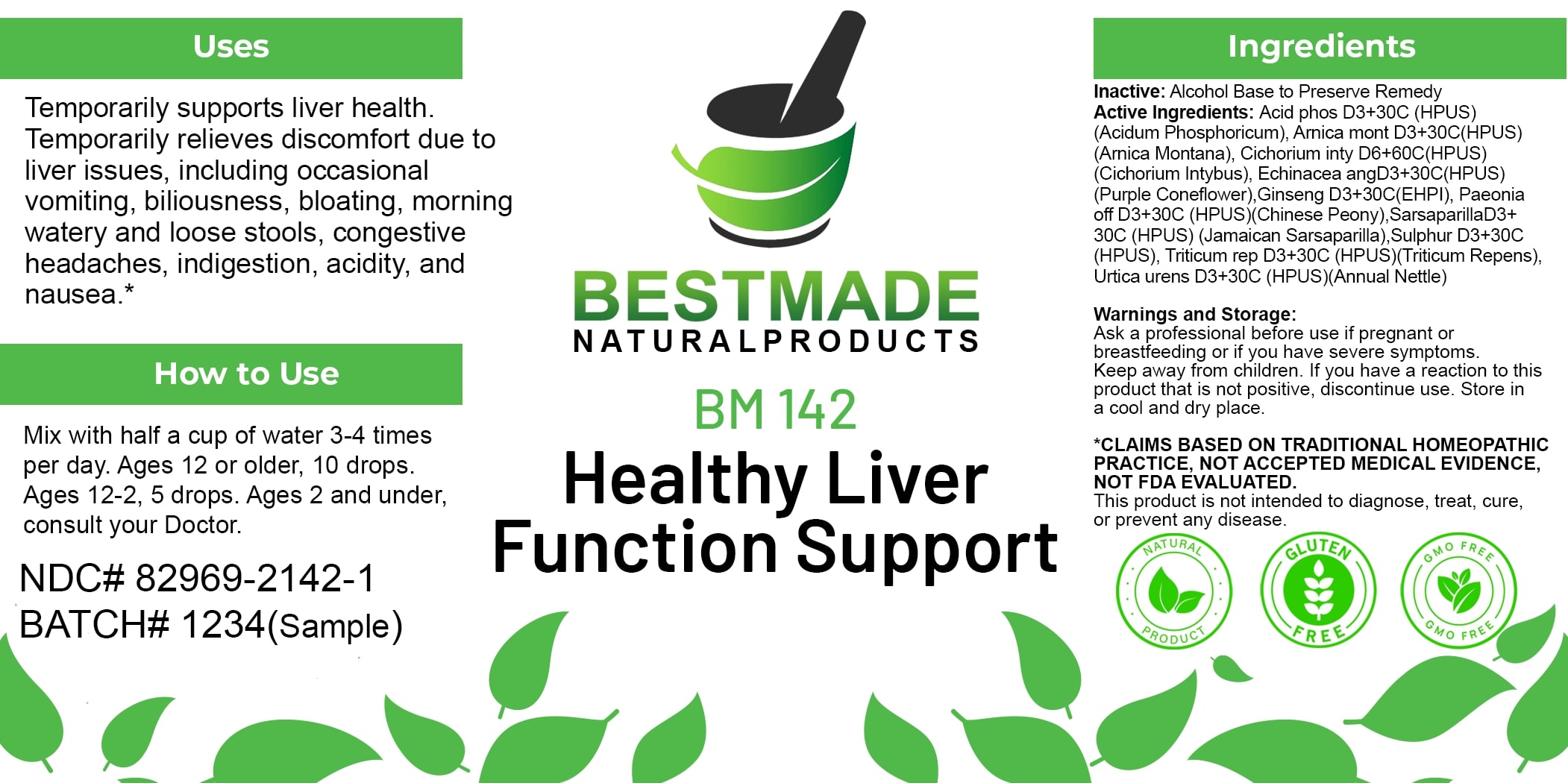 DRUG LABEL: Bestmade Natural Products BM142
NDC: 82969-2142 | Form: LIQUID
Manufacturer: Bestmade Natural Products
Category: homeopathic | Type: HUMAN OTC DRUG LABEL
Date: 20250218

ACTIVE INGREDIENTS: CHICORY ROOT 30 [hp_C]/30 [hp_C]; SARSAPARILLA 30 [hp_C]/30 [hp_C]; ELYMUS REPENS ROOT 30 [hp_C]/30 [hp_C]; SULFUR 30 [hp_C]/30 [hp_C]; PHOSPHORIC ACID 30 [hp_C]/30 [hp_C]; ECHINACEA ANGUSTIFOLIA 30 [hp_C]/30 [hp_C]; URTICA URENS 30 [hp_C]/30 [hp_C]; ARNICA MONTANA 30 [hp_C]/30 [hp_C]; PANAX QUINQUEFOLIUS WHOLE 30 [hp_C]/30 [hp_C]; PAEONIA OFFICINALIS ROOT 30 [hp_C]/30 [hp_C]
INACTIVE INGREDIENTS: ALCOHOL 30 [hp_C]/30 [hp_C]

BM142

DOSAGE AND ADMINISTRATION

How to Use

Mix with half a cup of water 3-4 times per day. Ages 12 or older, 10 drops. Ages 12-2, 5 drops. Ages 2 and under, consult your Doctor.

INACTIVE INGREDIENT

Ingredients

Inactive: Alcohol Base to Preserve Remedy

ACTIVE INGREDIENT

Active Ingredients: Acid phos D3+30C (HPUS) (Acidum Phosphoricum), Arnica mont D3+30C (HPUS) (Arnica Montana), Cichorium inty D6+60C (HPUS) (Cichorium Intybus), Echinacea ang D3+30C (HPUS) (Purple Coneflower), Ginseng D3+30C (EHPI), Paeonia off D3+30C (HPUS) (Chinese Peony), SarsaparillaD3+ 30C (HPUS) (Jamaican Sarsaparilla), Sulphur D3+30C (HPUS), Trillium rep D3+30C (HPUS) (Trillium Repens), Urtica urens D3+30C (HPUS) (Annual Nettle)

Uses

Temporarily supports liver health. Temporarily relieves discomfort due to liver issues, including occasional vomiting, biliousness, bloating, morning watery and loose stools, congestive headaches, indigestion, acidity, and nausea.*

*CLAIMS BASED ON TRADITIONAL HOMEOPATHIC PRACTICE, NOT ACCEPTED MEDICAL EVIDENCE. NOT FDA EVALUATED.

This product is not intended to diagnose, treat, cure, or prevent any disease.

Uses

Temporarily supports liver health. Temporarily relieves discomfort due to liver issues, including occasional vomiting, biliousness, bloating, morning watery and loose stools, congestive headaches, indigestion, acidity, and nausea.*

*CLAIMS BASED ON TRADITIONAL HOMEOPATHIC PRACTICE, NOT ACCEPTED MEDICAL EVIDENCE. NOT FDA EVALUATED.

This product is not intended to diagnose, treat, cure, or prevent any disease.

KEEP OUT OF REACH OF CHILDREN

Warnings and Storage:

Ask a professional before use if pregnant or breastfeeding or if you have severe symptoms. Keep away from children. If you have a reaction to this product that is not positive, discontinue use. Store in a cool and dry place.

Warnings and Storage:

Ask a professional before use if pregnant or breastfeeding or if you have severe symptoms. Keep away from children. If you have a reaction to this product that is not positive, discontinue use. Store in a cool and dry place.

*CLAIMS BASED ON TRADITIONAL HOMEOPATHIC PRACTICE, NOT ACCEPTED MEDICAL EVIDENCE. NOT FDA EVALUATED.

This product is not intended to diagnose, treat, cure, or prevent any disease.

Entire package label